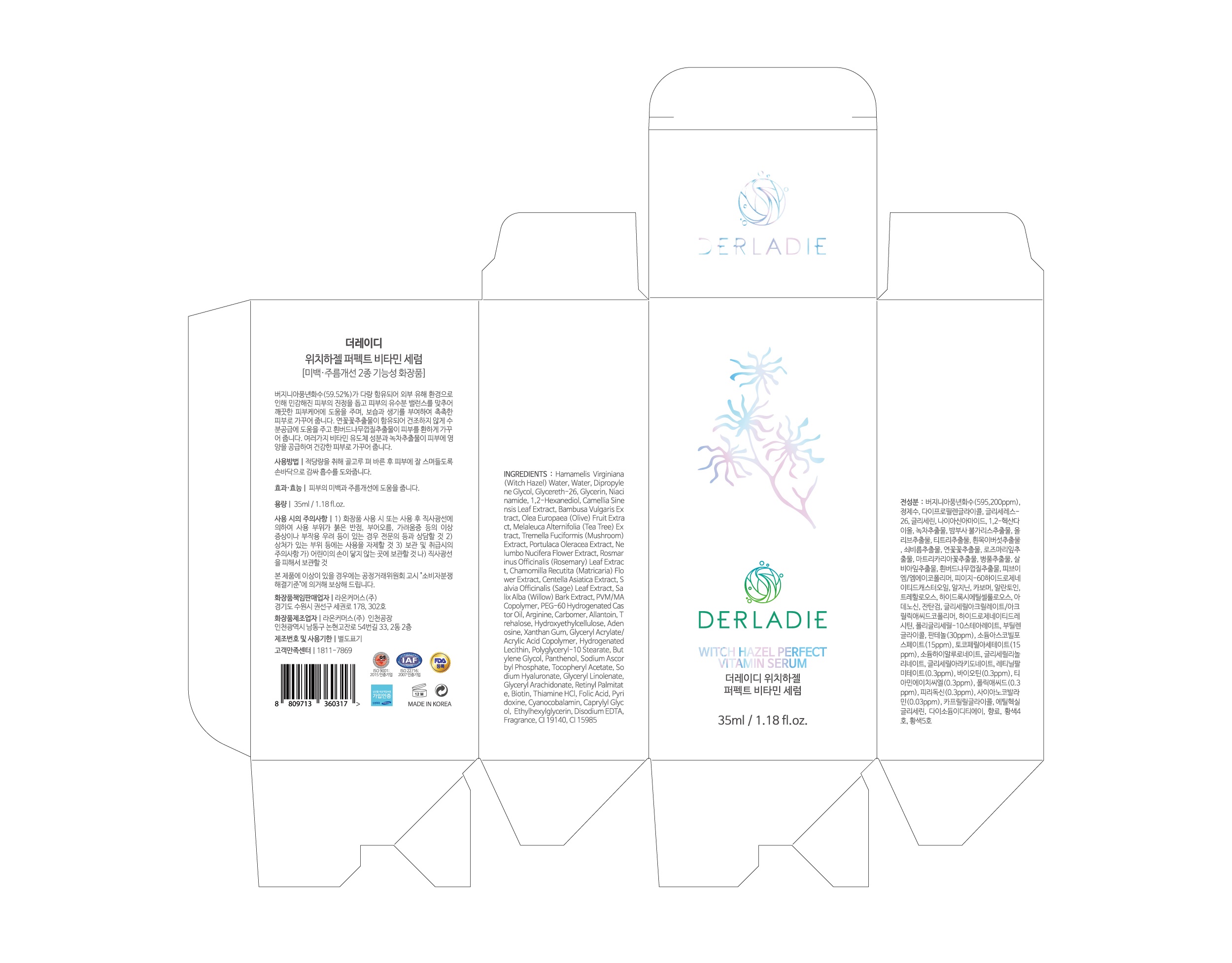 DRUG LABEL: DERLADIE WITCH HAZEL PERFECT VITAMIN SERUM
NDC: 82083-0002 | Form: LIQUID
Manufacturer: LAON COMMERCE co ltd
Category: otc | Type: HUMAN OTC DRUG LABEL
Date: 20210718

ACTIVE INGREDIENTS: ADENOSINE 0.04 g/100 mL; NIACINAMIDE 2 g/100 mL
INACTIVE INGREDIENTS: WATER

ACTIVE INGREDIENT

niacinamide, allantoin

INACTIVE INGREDIENT

Hamamelis Virginiana (Witch Hazel) Water
Water
Dipropylene Glycol
Glycereth-26
Glycerin
Niacinamide
1,2-Hexanediol
Camellia Sinensis Leaf Extract
Bambusa Vulgaris Extract
Olea Europaea (Olive) Fruit Extract
Melaleuca Alternifolia (Tea Tree) Extract
Tremella Fuciformis (Mushroom) Extract
Portulaca Oleracea Extract
Nelumbo Nucifera Flower Extract
Rosmarinus Officinalis (Rosemary) Leaf Extract
Chamomilla Recutita (Matricaria) Flower Extract
Centella Asiatica Extract
Salvia Officinalis (Sage) Leaf Extract
Salix Alba (Willow) Bark Extract
PVM/MA Copolymer
PEG-60 Hydrogenated Castor Oil
Arginine
Carbomer
Allantoin
Trehalose
Hydroxyethylcellulose
Adenosine
Xanthan Gum
Glyceryl Acrylate/Acrylic Acid Copolymer
Hydrogenated Lecithin
Polyglyceryl-10 Stearate
Butylene Glycol
Panthenol
Sodium Ascorbyl Phosphate
Tocopheryl Acetate
Sodium Hyaluronate
Glyceryl Linolenate
Glyceryl Arachidonate
Retinyl Palmitate
Biotin
Thiamine HCl
Folic Acid
Pyridoxine
Cyanocobalamin
Caprylyl Glycol
Ethylhexylglycerin
Disodium EDTA
Fragrance
CI 19140
CI 15985

Hamamelis Virginiana (Witch Hazel) Water
Water
Dipropylene Glycol
Glycereth-26
Glycerin
Niacinamide
1,2-Hexanediol
Camellia Sinensis Leaf Extract
Bambusa Vulgaris Extract
Olea Europaea (Olive) Fruit Extract
Melaleuca Alternifolia (Tea Tree) Extract
Tremella Fuciformis (Mushroom) Extract
Portulaca Oleracea Extract
Nelumbo Nucifera Flower Extract
Rosmarinus Officinalis (Rosemary) Leaf Extract
Chamomilla Recutita (Matricaria) Flower Extract
Centella Asiatica Extract
Salvia Officinalis (Sage) Leaf Extract
Salix Alba (Willow) Bark Extract
PVM/MA Copolymer
PEG-60 Hydrogenated Castor Oil
Arginine
Carbomer
Allantoin
Trehalose
Hydroxyethylcellulose
Adenosine
Xanthan Gum
Glyceryl Acrylate/Acrylic Acid Copolymer
Hydrogenated Lecithin
Polyglyceryl-10 Stearate
Butylene Glycol
Panthenol
Sodium Ascorbyl Phosphate
Tocopheryl Acetate
Sodium Hyaluronate
Glyceryl Linolenate
Glyceryl Arachidonate
Retinyl Palmitate
Biotin
Thiamine HCl
Folic Acid
Pyridoxine
Cyanocobalamin
Caprylyl Glycol
Ethylhexylglycerin
Disodium EDTA
Fragrance
CI 19140
CI 15985

PURPOSE

Skin whitening, wrinkle care

WARNINGS

■ if following abnormal symptoms persist, discontinue use

Irritation around the eyes, ears, mucous membranes, including the mouth, under the skin irritation and rashes

■ Stop immediately and consult a doctor if you experience

1) Hypersensitivity symptoms such as erythema, itching and dermatitis.

2) Skin Irritation

3) Following Instructions when using medication

(1) For external use only (Do not use internally)

(2) Avoid getting into the eyes (if contact occurs, wash well with clean water)

Keep Out of Reach of Children.

INDICATIONS AND USAGE

apply where needed

DOSAGE AND ADMINISTRATION

for external use only